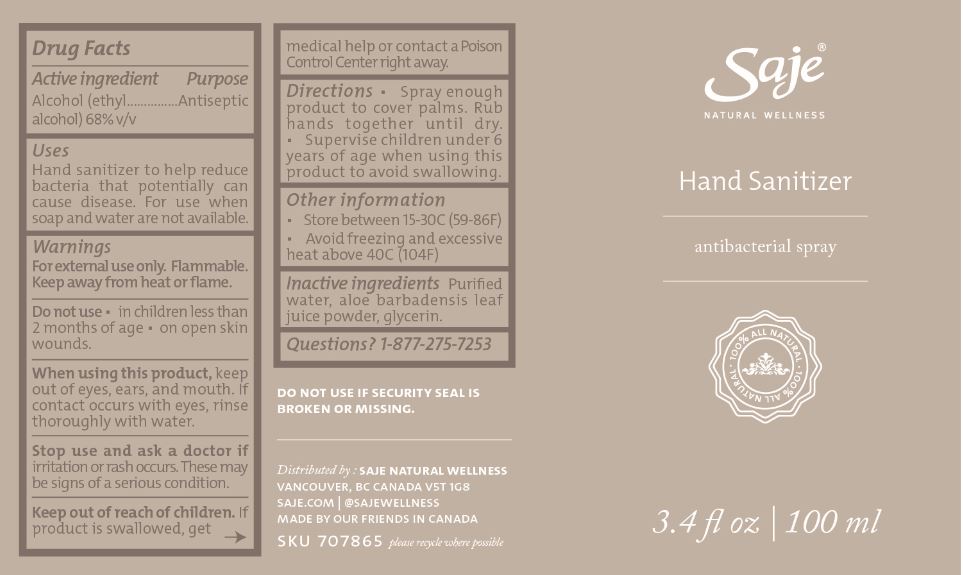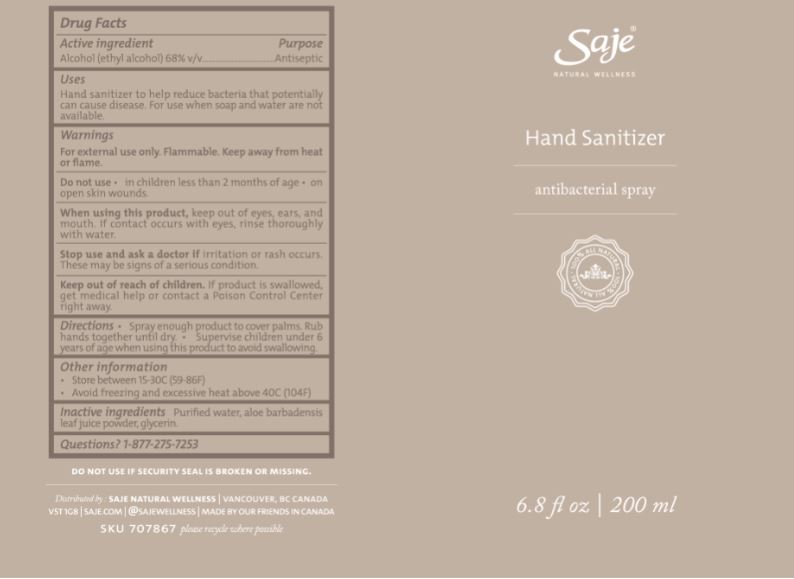 DRUG LABEL: Hand Sanitizer
NDC: 69204-025 | Form: SPRAY
Manufacturer: Natures Formulae Health Products Ltd.
Category: otc | Type: HUMAN OTC DRUG LABEL
Date: 20241217

ACTIVE INGREDIENTS: ALCOHOL 68 mL/100 mL
INACTIVE INGREDIENTS: GLYCERIN; ALOE VERA LEAF; WATER

Active Ingredient(s)

Alcohol 68% v/v. Purpose: Antiseptic

Purpose

Antiseptic, Hand Sanitizer

Product Identity

Hand Sanitizer - Antibacterial Spray

3.4 fl oz | 100 ml
6.8 fl oz | 200 ml

Use

Hand Sanitizer to help reduce bacteria that potentially can cause disease. For use when soap and water are not available.

Warnings

For external use only. Flammable. Keep away from heat or flame

Do not use

- in children less than 2 months of age
- on open skin wounds

When using this product keep out of eyes, ears, and mouth. If contact occurs with eyes, rinse thoroughly with water.
Stop use and ask a doctor if irritation or rash occurs. These may be signs of a serious condition.
Keep out of reach of children. If swallowed, contact a Poison Control Center right away or get medical help right away.

Stop use and ask a doctor if irritation or rash occurs. These may be signs of a serious condition.

Keep out of reach of children. If swallowed, get medical help or contact a Poison Control Center right away.

Directions

- Spray enough product on hands to cover all surfaces. Rub hands together until dry.
- Supervise children under 6 years of age when using this product to avoid swallowing.

Other information

- Store between 15-30C (59-86F)
- Avoid freezing and excessive heat above 40C (104F)

Inactive ingredients

purified water, aloe barbadensis leaf juice powder, glycerin.

Hand Sanitizer Spray - Package Label

100 mL NDC: 70983-025-01

200 mL NDC: 70983-025-02